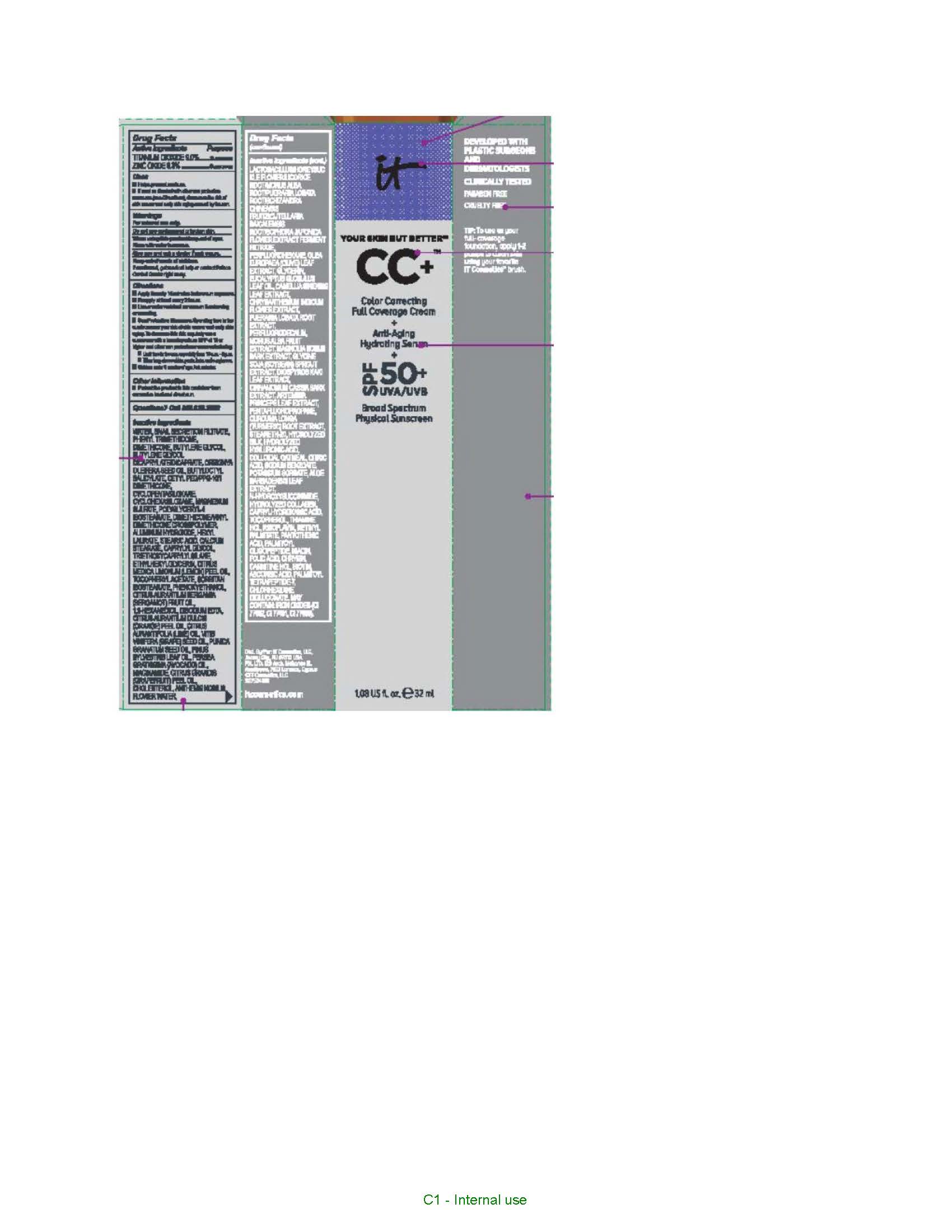 DRUG LABEL: it cosmetics Your Skin But Better CC Plus Color Correcting Broad Spectrum SPF 50 Plus Sunscreen Full Coverage Medium Tan Warm Neutral Rich Deep Bronze Neutral Deep Deep Bronze
NDC: 69259-7522 | Form: CREAM
Manufacturer: IT COSMETICS, LLC
Category: otc | Type: HUMAN OTC DRUG LABEL
Date: 20251218

ACTIVE INGREDIENTS: TITANIUM DIOXIDE 90 mg/1 mL; ZINC OXIDE 63 mg/1 mL
INACTIVE INGREDIENTS: WATER; PHENYL TRIMETHICONE; DIMETHICONE; BUTYLENE GLYCOL; BUTYLENE GLYCOL DICAPRYLATE/DICAPRATE; BUTYLOCTYL SALICYLATE; CETYL PEG/PPG-10/1 DIMETHICONE (HLB 1.5); CYCLOMETHICONE 5; CYCLOMETHICONE 6; MAGNESIUM SULFATE, UNSPECIFIED FORM; POLYGLYCERYL-4 ISOSTEARATE; DIMETHICONE/VINYL DIMETHICONE CROSSPOLYMER (HARD PARTICLE); ALUMINUM HYDROXIDE; HEXYL LAURATE; STEARIC ACID; CALCIUM STEARATE; CAPRYLYL GLYCOL; TRIETHOXYCAPRYLYLSILANE; ETHYLHEXYLGLYCERIN; LEMON OIL; .ALPHA.-TOCOPHEROL ACETATE, D-; SORBITAN; ISOSTEARETH-5; PHENOXYETHANOL; BERGAMOT OIL; 1,2-HEXANEDIOL; EDETATE DISODIUM; ORANGE OIL; LIME OIL; GRAPE SEED OIL; PUNICA GRANATUM SEED OIL; PINE NEEDLE OIL (PINUS SYLVESTRIS); AVOCADO OIL; NIACINAMIDE; CITRUS MAXIMA FRUIT RIND OIL; CHOLESTEROL; PERFLEXANE; GLYCERIN; EUCALYPTUS OIL; GREEN TEA LEAF; PERFLUNAFENE; STEARETH-20; CITRIC ACID MONOHYDRATE; SODIUM BENZOATE; POTASSIUM SORBATE; ALOE VERA LEAF; N-HYDROXYSUCCINIMIDE; CAPRYLHYDROXAMIC ACID; TOCOPHEROL; THIAMINE HYDROCHLORIDE; RIBOFLAVIN; VITAMIN A PALMITATE; PANTOTHENIC ACID; PALMITOYL TRIPEPTIDE-1; NIACIN; FOLIC ACID; CHRYSIN; LEVOCARNITINE HYDROCHLORIDE; BIOTIN; ASCORBIC ACID; PALMITOYL TETRAPEPTIDE-7; CHLORHEXIDINE GLUCONATE; FERRIC OXIDE RED

Active ingredients

Titanium dioxide 9.0%

Zinc oxide 6.3%%

Purpose

Sunscreen

Uses

- helps prevent sunburn
- if used as directed with other sun protection measures (see Directions), decreases the risk of skin cancer and early skin aging caused by the sun

Warnings

For external use only

Do not use

on damaged or broken skin

When using this product

keep out of eyes. Rinse with water to remove.

Stop use and ask a doctor if

rash occurs

Keep out of reach of children.

If swallowed, get medical help or contact a Poison Control Center right away.

Directions

For sunscreen use:
● apply liberally 15 minutes before sun exposure
● reapply at least every 2 hours
● use a water resistant sunscreen if swimming or sweating
● Sun Protection Measures. Spending time in the sun increases your risk of skin cancer and early skin aging. To decrease this risk, regularly use a sunscreen with a Broad Spectrum SPF value of 15 or higher and other sun protection measures including:
● limit time in the sun, especially from 10 a.m. – 2 p.m.
● wear long-sleeved shirts, pants, hats, and sunglasses
● children under 6 months of age: Ask a doctor

Other information

protect the product in this container from excessive heat and direct sun

Inactive ingredients

water, snail secretion filtrate, phenyl trimethicone, dimethicone, butylene glycol, butylene glycol dicaprylated/dicaprate, orbignya oleifera seed oil, butyloctyl salicylate, cetyl PEG/PPG-10/1 dimethiocone, cyclopentasiloxane, cyclohexasiloxane, magnesium sulfate, polyglyceryl-4 isostearate, dimethicone/vinyl dimethicone crosspolymer, aluminum hydroxide, hexyl laurate, stearic acid, calcium stearate, caprylyl glycol, triethoxycaprylylsilane, ethylhexylglycerin, citrus medica limonum (lemon) peel oil, tocopheryl acetate, sorbitan isostearate, phenoxyethanol, citrus aurantium bergamia (bergamot) fruit oil, 1,2-hexanediol, disodium EDTA, citrus aurantium dulcis (orange) peel oil, cirus aurantifolia (lime) oil vitis vinifera (grape) seed oil, punica gratissiima (avocado) oil, niacinamide, citrus grandis (grapefuit) peel oil, chloesterol, anthemis b=nobilis flower water, lactobacillius/honeysuckle flowr/locorice root/morus alba root/pueraria lobata root/schizandra chinensis fruit/scutellaria baicalensis root/sophora japonica flower extract ferment filtrate, perfluorohexane, olea europaea (olive) leaf extract, glycerin, eucalyptus globulus leaf oil, camellia sinensis leaf extract, chrysanthemium indicum flower extract, pueraria lobata root extract, perfluorodecalin, morus alba gruit extract, magnolia kobus bark extract, glycine soja (soybean) sprout extract, diospyros kaki leaf extract, cinnamomum cassia bark extract, artemisia princeps leaf extract, epntafluoropropane, curcuma longa (turmeric) root extract, steareth-20, hydrolyzed silk, hydrolyzed hyaluronic acid, colloidal oatmeal, citric acid, sodium benzoate, potassum sorbate, aloe barbadensis leaf extract, n-hydroxysuccinimide, hydrolyzed collagen, caprylhydroxamic acid, tocopherol, thiamine HCL, riboflavin, retinyl palmitate, pantothenic acid, palmitoyl oligopeptide, nicin, folic acid, chrysin, carnitine HCL, biotin, ascorbic acid, palmitoyl tetrapeptide-7, chlorhexidine digluconate; may contain: iron oxides

Questions or comments?

Call 800-620-3950